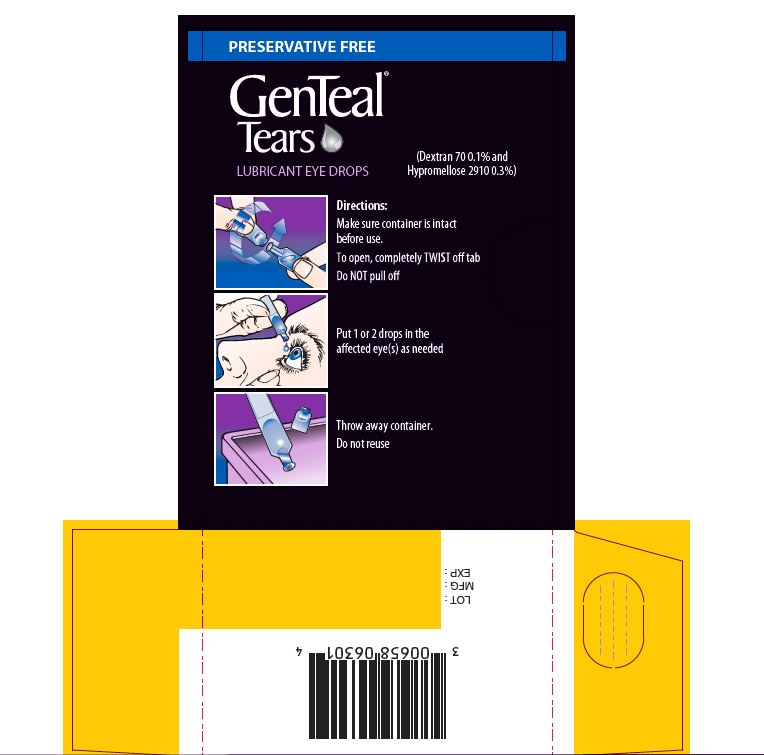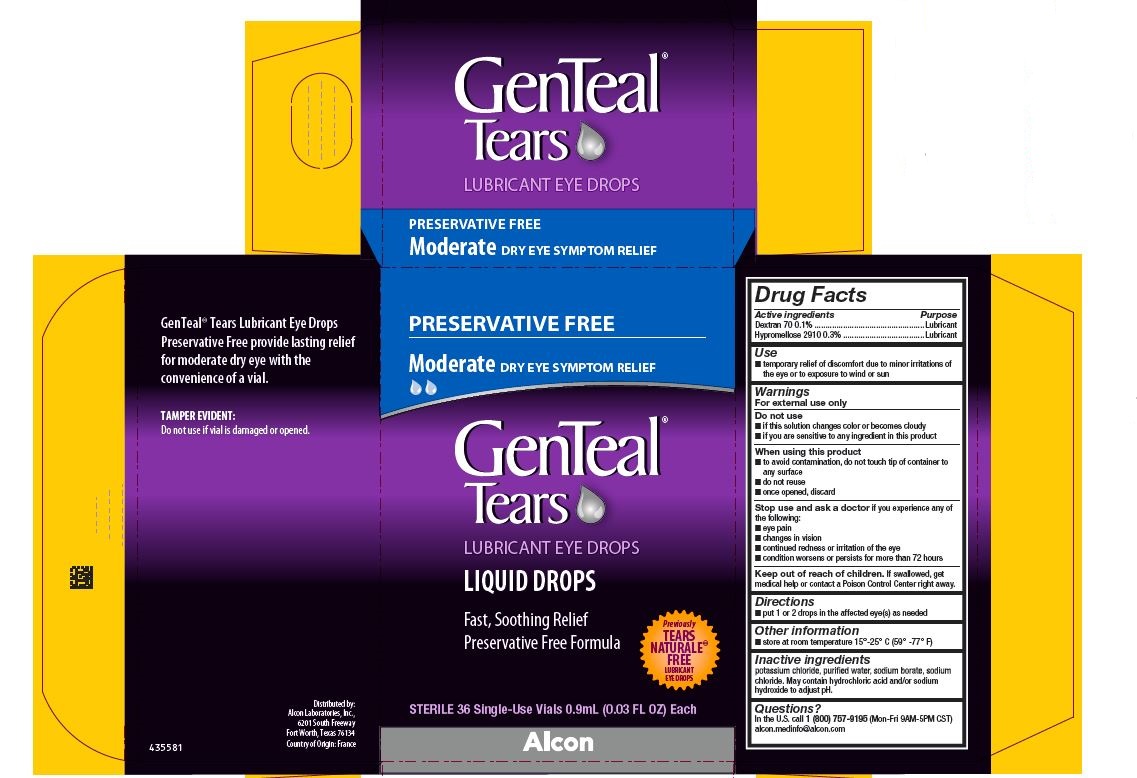 DRUG LABEL: GenTeal Tears Moderate Preservative Free
NDC: 0065-8063 | Form: SOLUTION/ DROPS
Manufacturer: Alcon Laboratories, Inc.
Category: otc | Type: HUMAN OTC DRUG LABEL
Date: 20231214

ACTIVE INGREDIENTS: Hypromellose 2910 (4000 Mpa.s) 3 mg/1 mL; Dextran 70 1 mg/1 mL
INACTIVE INGREDIENTS: Potassium Chloride; Water; Sodium Borate; Hydrochloric Acid; Sodium Hydroxide; Sodium Chloride

Drug Facts

ACTIVE INGREDIENT

Active Ingredients | Purpose
Dextran 70 0.1% | Lubricant
Hypromellose 2910 0.3% | Lubricant

Uses

- temporary relief of discomfort due to minor irritations of the eye, or to exposure to wind or sun

Warnings

For external use only

Do not use

- if this solution changes color or becomes cloudy
- if you are sensitive to any ingredient in this product

When using this product

- to avoid contamination, do not touch tip of container to any surface
- do not reuse
- once opened, discard

Stop use and ask a doctor if

you experience any of the following:

- eye pain
- changes in vision
- continued redness or irritation of the eye
- condition worsens or persists for more than 72 hours

Keep out of reach of children.

If swallowed, get medical help or contact a Poison Control Center right away.

Directions

- put 1 or 2 drops in the affected eye(s) as needed.

Other information

- store are room temperature 15o – 25o C (59o – 77o F)

Inactive ingredients

potassium chloride, purified water, sodium borate, sodium chloride. May contain hydrochloric acid and/or sodium hydroxide to adjust pH.

Questions?

In the U.S. call 1 (800) 757-9195 (Mon-Fri 9AM-5PM CST)
alcon.medinfo@alcon.com

PRINCIPAL DISPLAY PANEL

PRESERVATIVE FREE
Moderate DRY EYE SYMPTOM RELIEF
GenTeal® Tears
LUBRICANT EYE DROPS
LIQUID DROPS
Fast, Soothing Relief
Preservative Free Formula
Previously TEARS NATURALE® FREE LUBRICANT EYE DROPS
STERILE 36 Single-Use Vials 0.9 mL (0.03 FL OZ) Each
Alcon
GenTeal® Tears Lubricant Eye Drops
Preservative Free provide lasting relief
for moderate dry eye with the
convenience of a vial.
TAMPER EVIDENTY:
Do not use if vial is damaged or opened.
Distributed by:
Alcon Laboratories, Inc.,
6201 South Freeway
Fort Worth, Texas 76134
Country of Origin: France
435581